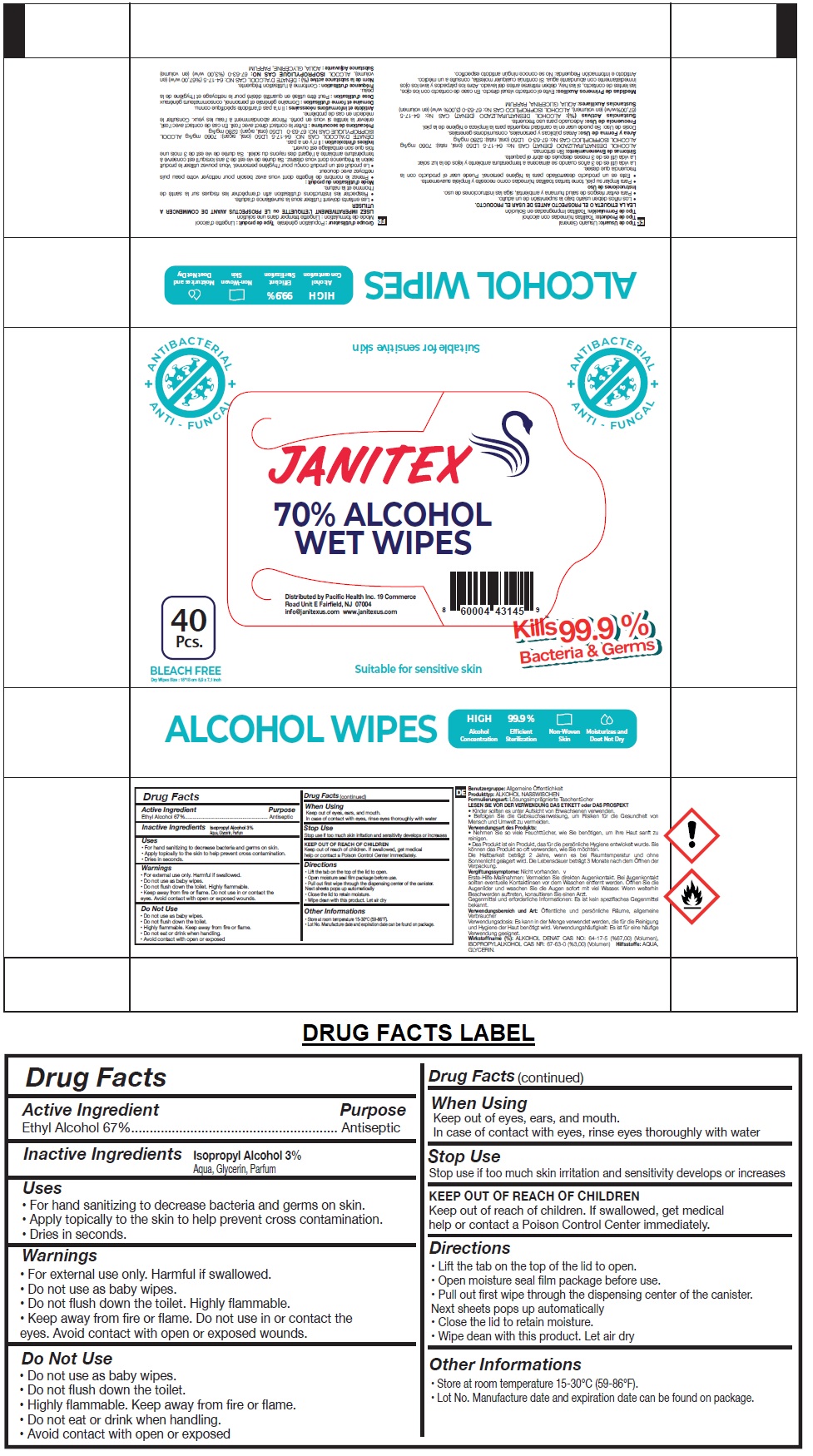 DRUG LABEL: JANITEX ALCOHOL WET WIPES 70%
NDC: 79519-030 | Form: CLOTH
Manufacturer: Pacific Health Systems Inc.
Category: otc | Type: HUMAN OTC DRUG LABEL
Date: 20200819

ACTIVE INGREDIENTS: ALCOHOL 67 mL/100 mL
INACTIVE INGREDIENTS: ISOPROPYL ALCOHOL; WATER; GLYCERIN

JANITEX 70% ALCOHOL WET WIPES

Active Ingredient

Ethyl Alcohol 67%

Purpose

Antiseptic

Inactive Ingredients Isopropyl Alcohol 3%, Aqua, Glycerin, Parfum

Uses

• For hand sanitizing to decrease bacteria and germs on skin.

• Apply topically to the skin to help prevent cross contamination.

• Dries in seconds.

Warnings

• For external use only. Harmful if swallowed.

• Do not use as baby wipes.

• Do not flush down the toilet. Highly flammable.

• Keep away from fire or flame. Do not use in or contact the eyes. Avoid contact with open or exposed wounds.

Do not Use

• Do not use as baby wipes.

• Do not flush down the toilet.

• Highly flammable. Keep away from fire or flame.

• Do not eat or drink when handling.

• Avoid contact with open or exposed

When Using

Keep out of eyes, ears, and mouth.

In case of contact with eyes, rinse eyes thoroughly with water

Stop Use

Stop use if too much skin irritation and sensitivity develops or increases

Keep out of reach of children. If swallowed, get medical help or contact a Poison Control Center immediately.

Directions

• Lift the tab on the top of the lid to open.

• Open moisture seal film package before use.

• Pull out first wipe through the dispensing center of the canister. Next sheets pops up automatically

• Close the lid to retain moisture.

• Wipe dean with this product. Let air dry

Other Informations

• Store at room temperature 15-30°C (59-86°F).

• Lot No. Manufacture date and expiration date can be found on package.

+ ANTIBACTERIAL + ANTI - FUNGAL

BLEACH FREE

Dry Wipes Size: 15*18 cm 5,9 x 7,1 inch

Suitable for sensitive skin

Kills 99.9% Bacteria & Germs

ALCOHOL WIPES

Alcohol Concentration

Efficient Sterilization

Non-Woven Skin

Moisturizes and Does Not Dry

Distributed by Pacific Health Inc. 19 Commerce

Road Unit E Fairfield, NJ 07004

info@janitexus.com www.janitexus.com